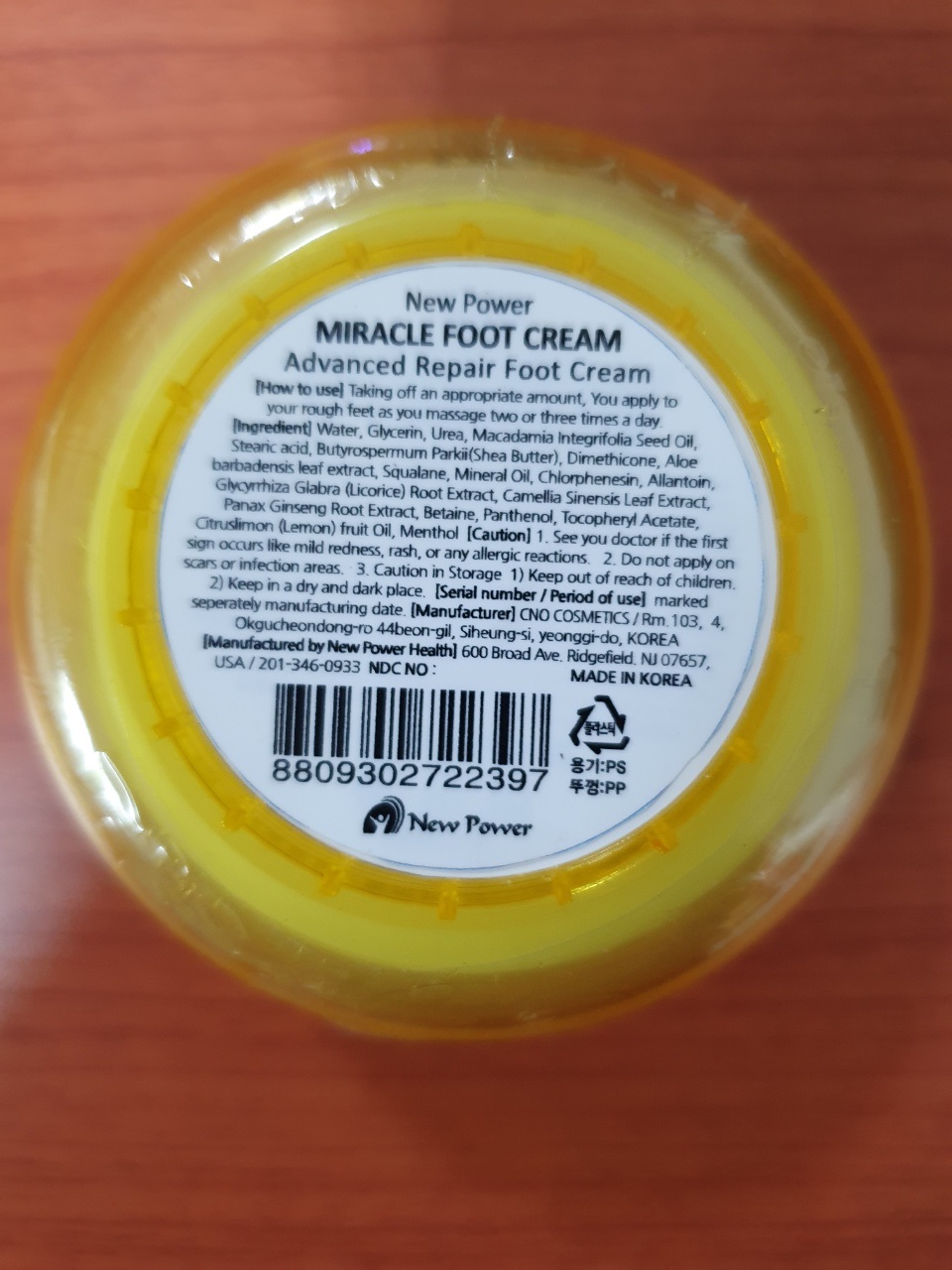 DRUG LABEL: Miracle FootCream Lemon
NDC: 82145-0006 | Form: CREAM
Manufacturer: Aloe Vera Korea Co.,Ltd.
Category: otc | Type: HUMAN OTC DRUG LABEL
Date: 20220328

ACTIVE INGREDIENTS: EDETATE DISODIUM 0.05 g/100 g; UREA 4 g/100 g; ALOE VERA LEAF 0.5 g/100 g; GLYCERIN 8 g/100 g
INACTIVE INGREDIENTS: WATER

Drug Facts

ACTIVE INGREDIENT

urea, glycerin, aloe barbadensis leaf extract, disodium edta

INACTIVE INGREDIENT

Water, macadamia ternifolia seed oil, stearic acid, shea butter, etc

PURPOSE

dead skin cell care cream

keep out of reach of the children

INDICATIONS AND USAGE

taking off an appropriate amount

you apply to your rough feet as you massage two or three times a day

WARNINGS

don’t use on the part where there is injury, eczema, or dermatitis

if swallowed, get medical help or contact a person control center immediately

DOSAGE AND ADMINISTRATION

for topical use only